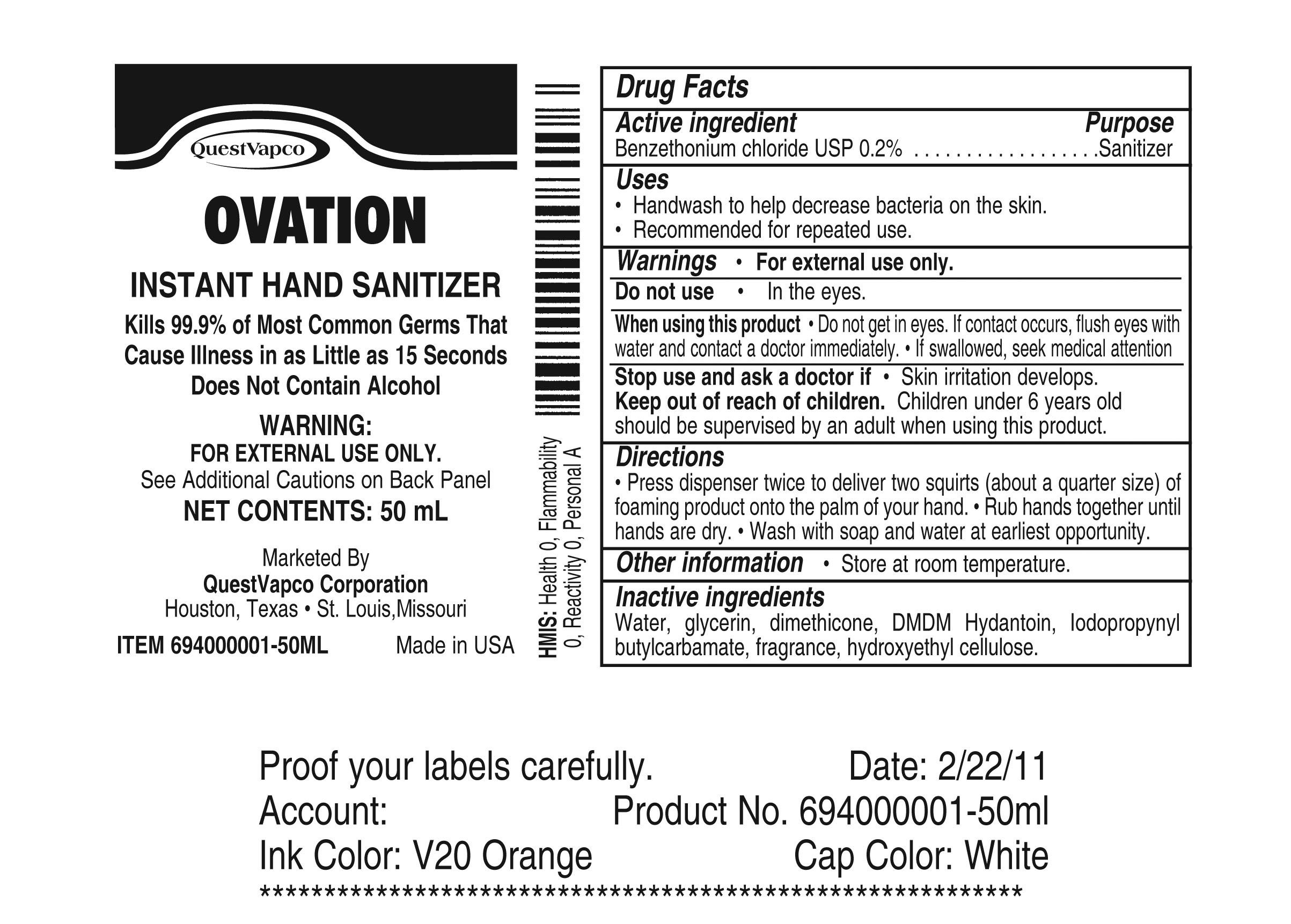 DRUG LABEL: Ovation
NDC: 67858-001 | Form: LIQUID
Manufacturer: QuestVapco Corporation
Category: otc | Type: HUMAN OTC DRUG LABEL
Date: 20110620

ACTIVE INGREDIENTS: Benzethonium chloride 1 mg/50 mL
INACTIVE INGREDIENTS: Water; Hydroxypropyl cellulose; Glycerin; Dimethicone; dmdm hydantoin; Sodium Hydroxide

Drug Facts

Active Ingredient

Benzenethonium chloride USP 0.2%

Purpose

Sanitizer

Uses

Handwash to help decrease bacteria on the skin.

Recommended for repeated use.

Warnings

For external use only

Do Not Use

In the eyes.

When using this product

Do not get in eyes. If contact occurs, flush eyes with water and contact a doctor immediately. If swallowed, seek medical attention.

Stop use and ask a doctor if

Skin irritation develops.

Keep out of reach of children.

Children under 6 years old should be supervised by an adult when using this product.

Inactive ingredients

Water, glycerin, dimethicone, DMDM Hydantoin, isdopropynyl butylcarbamate, fragrance, hydroxyethyl cellulose

Directions

Press dispenser twice to deliver two squirts (about a quarter size) of foaming product onto the palm of your hand. Rub hands together until hands are dry. Wash with soap and water at earliest opportunity.